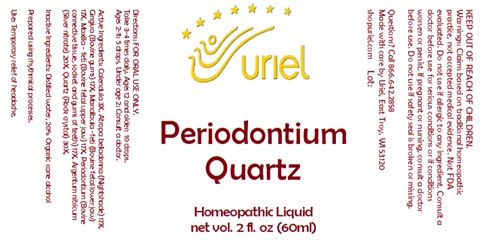 DRUG LABEL: Periodontium Quartz
NDC: 48951-8415 | Form: LIQUID
Manufacturer: Uriel Pharmacy, Inc.
Category: homeopathic | Type: HUMAN OTC DRUG LABEL
Date: 20241024

ACTIVE INGREDIENTS: SUS SCROFA TOOTH 17 [hp_X]/1 mL; SILICA 30 [hp_X]/1 mL; ATROPA BELLADONNA 17 [hp_X]/1 mL; BEEF TONGUE 17 [hp_X]/1 mL; CALENDULA OFFICINALIS FLOWERING TOP 3 [hp_X]/1 mL; BOS TAURUS BONE 17 [hp_X]/1 mL; SILVER NITRATE 20 [hp_X]/1 mL
INACTIVE INGREDIENTS: WATER; ALCOHOL

Periodontium Quartz

INDICATIONS AND USAGE

Directions: FOR ORAL USE ONLY.

DOSAGE AND ADMINISTRATION

Take 3-4 times daily. Ages 12 and older: 10 drops.
Ages 2-11: 5 drops. Under age 2: Consult a doctor.

ACTIVE INGREDIENT

Active Ingredients: Calendula 3X, Atropa belladonna (Nightshade) 17X, Gingiva (Bovine gums) 17X, Mandibula -feti (Bovine fetal lower jaw) 17X, Maxilla - feti (Bovine fetal upper jaw) 17X, Periodontium (Bovine connective tissue, socket and gums of teeth) 17X, Argentum nitricum (Silver nitrate) 20X, Quartz (Rock crystal) 30X,

Inactive Ingredients: Distilled water, 20% Organic cane alcohol

Prepared using rhythmical processes

PURPOSE

Use: Temporary relief of headache.

KEEP OUT OF REACH OF CHILDREN.

WARNINGS

Warnings: Claims based on traditional homeopathic practice, not accepted medical evidence. Not FDA evaluated. Do not use if allergic to any ingredient. Consult a doctor before use for serious conditions or if conditions worsen or persist. If pregnant or nursing, consult a doctor before use. Do not use if safety seal is broken or missing.

Questions? Call 866.642.2858
Made with care by Uriel, East Troy, WI 53120
shopuriel.com Lot: